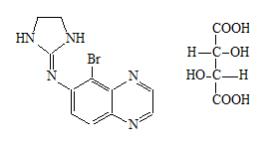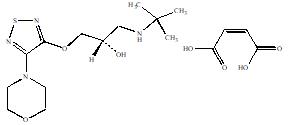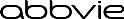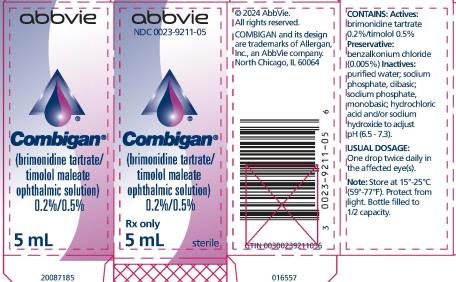 DRUG LABEL: COMBIGAN
NDC: 0023-9211 | Form: SOLUTION/ DROPS
Manufacturer: Allergan, Inc.
Category: prescription | Type: HUMAN PRESCRIPTION DRUG LABEL
Date: 20240726

ACTIVE INGREDIENTS: brimonidine tartrate 2 mg/1 mL; timolol maleate 5 mg/1 mL
INACTIVE INGREDIENTS: BENZALKONIUM CHLORIDE; sodium phosphate, monobasic; sodium phosphate, dibasic; water; hydrochloric acid; sodium hydroxide

HIGHLIGHTS OF PRESCRIBING INFORMATION

These highlights do not include all the information needed to use COMBIGAN® safely and effectively. See full prescribing information for COMBIGAN®.
COMBIGAN® (brimonidine tartrate/timolol maleate ophthalmic solution) 0.2%/0.5%
For topical administration
Initial U.S. Approval: 2007

1 INDICATIONS AND USAGE

COMBIGAN® is an alpha-adrenergic receptor agonist with a beta-adrenergic receptor inhibitor indicated for the reduction of elevated intraocular pressure (IOP) in patients with glaucoma or ocular hypertension who require adjunctive or replacement therapy due to inadequately controlled IOP; the IOP-lowering of COMBIGAN® dosed twice a day was slightly less than that seen with the concomitant administration of timolol maleate ophthalmic solution, 0.5% dosed twice a day and brimonidine tartrate ophthalmic solution, 0.2% dosed three times per day. (1)

2 DOSAGE AND ADMINISTRATION

One drop in the affected eye(s), twice daily approximately 12 hours apart. (2)

3 DOSAGE FORMS AND STRENGTHS

Solution containing 2 mg/mL brimonidine tartrate and 5 mg/mL timolol. (3)

4 CONTRAINDICATIONS

- Bronchial asthma, a history of bronchial asthma, severe chronic obstructive pulmonary disease. (4.1, 5.1, 5.3)
- Sinus bradycardia, atrioventricular block, overt cardiac failure, cardiogenic shock. (4.2, 5.2)
- Neonates and infants (under the age of 2 years). (4.3)
- Hypersensitivity to any component of this product. (4.4)

5 WARNINGS AND PRECAUTIONS

- Potential for Severe Respiratory or Cardiac Reactions (5.1)
- Cardiac Failure (5.2)
- Obstructive Pulmonary Disease (5.3)
- Potentiation of Vascular Insufficiency (5.4)
- Increased Reactivity to Allergens (5.5)
- Potentiation of Muscle Weakness (5.6)
- Masking of Hypoglycemic Symptoms in Patients with Diabetes Mellitus (5.7)
- Masking of Thyrotoxicosis (5.8)
- Ocular Hypersensitivity (5.9)

6 ADVERSE REACTIONS

Most common adverse reactions occurring in approximately 5 to 15% of patients included allergic conjunctivitis, conjunctival folliculosis, conjunctival hyperemia, eye pruritus, ocular burning, and stinging. (6.1)

To report SUSPECTED ADVERSE REACTIONS, contact AbbVie at 1-800-678-1605 or the FDA at 1-800-FDA-1088 or www.fda.gov/medwatch.

7 DRUG INTERACTIONS

- Antihypertensives/cardiac glycosides may lower blood pressure. (7.1)
- Concomitant use with systemic beta-blockers may potentiate systemic beta-blockade. (7.2)
- Oral or intravenous calcium antagonists may cause atrioventricular conduction disturbances, left ventricular failure, and hypotension. (7.3)
- Catecholamine-depleting drugs may have additive effects and produce hypotension and/or marked bradycardia. (7.4)
- Use with CNS depressants may result in an additive or potentiating effect. (7.5)
- Digitalis and calcium antagonists may have additive effects in prolonging atrioventricular conduction time. (7.6)
- CYP2D6 inhibitors may potentiate systemic beta-blockade. (7.7)
- Tricyclic antidepressants may potentially blunt the hypotensive effect of systemic clonidine. (7.8)
- Monoamine oxidase inhibitors may result in increased hypotension. (7.9)

8 USE IN SPECIFIC POPULATIONS

Not for use in children below the age of 2 years. Use with caution in children ≥ 2 years of age. (8.4)

FULL PRESCRIBING INFORMATION

1 INDICATIONS AND USAGE

COMBIGAN® (brimonidine tartrate/timolol maleate ophthalmic solution) 0.2%/0.5% is an alpha-adrenergic receptor agonist with a beta-adrenergic receptor inhibitor indicated for the reduction of elevated intraocular pressure (IOP) in patients with glaucoma or ocular hypertension who require adjunctive or replacement therapy due to inadequately controlled IOP; the IOP-lowering of COMBIGAN® dosed twice a day was slightly less than that seen with the concomitant administration of 0.5% timolol maleate ophthalmic solution dosed twice a day and 0.2% brimonidine tartrate ophthalmic solution dosed three times per day.

2 DOSAGE AND ADMINISTRATION

The recommended dose is one drop of COMBIGAN® in the affected eye(s) twice daily approximately 12 hours apart. If more than one topical ophthalmic product is to be used, the different products should be instilled at least 5 minutes apart.

3 DOSAGE FORMS AND STRENGTHS

Solution containing 2 mg/mL brimonidine tartrate and 5 mg/mL timolol (6.8 mg/mL timolol maleate).

4 CONTRAINDICATIONS

4.1 Reactive Airway Disease Including Asthma, COPD

COMBIGAN® is contraindicated in patients with reactive airway disease including bronchial asthma; a history of bronchial asthma; severe chronic obstructive pulmonary disease [see Warnings and Precautions (5.1, 5.3)].

4.2 Sinus Bradycardia, AV Block, Cardiac Failure, Cardiogenic Shock

COMBIGAN® is contraindicated in patients with sinus bradycardia; second or third degree atrioventricular block; overt cardiac failure [see Warnings and Precautions (5.2)]; cardiogenic shock.

4.3 Neonates and Infants (Under the Age of 2 Years)

COMBIGAN® is contraindicated in neonates and infants (under the age of 2 years).

4.4 Hypersensitivity Reactions

Local hypersensitivity reactions have occurred following the use of different components of COMBIGAN®. COMBIGAN® is contraindicated in patients who have exhibited a hypersensitivity reaction to any component of this medication in the past.

5 WARNINGS AND PRECAUTIONS

5.1 Potential for Severe Respiratory or Cardiac Reactions

COMBIGAN® contains timolol maleate; and although administered topically can be absorbed systemically. Therefore, the same types of adverse reactions found with systemic administration of beta-adrenergic blocking agents may occur with topical administration. For example, severe respiratory reactions and cardiac reactions including death due to bronchospasm in patients with asthma, and rarely death in association with cardiac failure have been reported following systemic or ophthalmic administration of timolol maleate [see Contraindications (4.1)]. Additionally, ophthalmic beta-blockers may impair compensatory tachycardia and increase risk of hypotension.

5.2 Cardiac Failure

Sympathetic stimulation may be essential for support of the circulation in individuals with diminished myocardial contractility, and its inhibition by beta-adrenergic receptor blockade may precipitate more severe failure.

In patients without a history of cardiac failure, continued depression of the myocardium with beta-blocking agents over a period of time can, in some cases, lead to cardiac failure. At the first sign or symptom of cardiac failure, COMBIGAN® should be discontinued [see Contraindications (4.2)].

5.3 Obstructive Pulmonary Disease

Patients with chronic obstructive pulmonary disease (e.g., chronic bronchitis, emphysema) of mild or moderate severity, bronchospastic disease, or a history of bronchospastic disease (other than bronchial asthma or a history of bronchial asthma, in which COMBIGAN® is contraindicated [see Contraindications (4.1)] should, in general, not receive beta-blocking agents, including COMBIGAN®.

5.4 Potentiation of Vascular Insufficiency

COMBIGAN® may potentiate syndromes associated with vascular insufficiency. COMBIGAN® should be used with caution in patients with depression, cerebral or coronary insufficiency, Raynaud’s phenomenon, orthostatic hypotension, or thromboangiitis obliterans.

5.5 Increased Reactivity to Allergens

While taking beta-blockers, patients with a history of atopy or a history of severe anaphylactic reactions to a variety of allergens may be more reactive to repeated accidental, diagnostic, or therapeutic challenge with such allergens. Such patients may be unresponsive to the usual doses of epinephrine used to treat anaphylactic reactions.

5.6 Potentiation of Muscle Weakness

Beta-adrenergic blockade has been reported to potentiate muscle weakness consistent with certain myasthenic symptoms (e.g., diplopia, ptosis, and generalized weakness). Timolol has been reported rarely to increase muscle weakness in some patients with myasthenia gravis or myasthenic symptoms.

5.7 Masking of Hypoglycemic Symptoms in Patients with Diabetes Mellitus

Beta-adrenergic blocking agents should be administered with caution in patients subject to spontaneous hypoglycemia or to diabetic patients (especially those with labile diabetes) who are receiving insulin or oral hypoglycemic agents. Beta-adrenergic receptor blocking agents may mask the signs and symptoms of acute hypoglycemia.

5.8 Masking of Thyrotoxicosis

Beta-adrenergic blocking agents may mask certain clinical signs (e.g., tachycardia) of hyperthyroidism. Patients suspected of developing thyrotoxicosis should be managed carefully to avoid abrupt withdrawal of beta-adrenergic blocking agents that might precipitate a thyroid storm.

5.9 Ocular Hypersensitivity

Ocular hypersensitivity reactions have been reported with brimonidine tartrate ophthalmic solutions 0.2%, with some reported to be associated with an increase in intraocular pressure [see Contraindications (4.4)].

5.10 Contamination of Topical Ophthalmic Products After Use

There have been reports of bacterial keratitis associated with the use of multiple-dose containers of topical ophthalmic products. These containers had been inadvertently contaminated by patients who, in most cases, had a concurrent corneal disease or a disruption of the ocular epithelial surface [see Patient Counseling Information (17)].

5.11 Impairment of Beta-adrenergically Mediated Reflexes During Surgery

The necessity or desirability of withdrawal of beta-adrenergic blocking agents prior to major surgery is controversial. Beta-adrenergic receptor blockade impairs the ability of the heart to respond to beta-adrenergically mediated reflex stimuli. This may augment the risk of general anesthesia in surgical procedures. Some patients receiving beta-adrenergic receptor blocking agents have experienced protracted severe hypotension during anesthesia. Difficulty in restarting and maintaining the heartbeat has also been reported. For these reasons, in patients undergoing elective surgery, some authorities recommend gradual withdrawal of beta-adrenergic receptor blocking agents.

If necessary during surgery, the effects of beta-adrenergic blocking agents may be reversed by sufficient doses of adrenergic agonists.

6 ADVERSE REACTIONS

6.1 Clinical Studies Experience

Because clinical studies are conducted under widely varying conditions, adverse reaction rates observed in the clinical studies of a drug cannot be directly compared to rates in the clinical studies of another drug and may not reflect the rates observed in practice.

COMBIGAN®

In clinical trials of 12 months duration with COMBIGAN®, the most frequent reactions associated with its use occurring in approximately 5% to 15% of the patients included: allergic conjunctivitis, conjunctival folliculosis, conjunctival hyperemia, eye pruritus, ocular burning, and stinging. The following adverse reactions were reported in 1% to 5% of patients: asthenia, blepharitis, corneal erosion, depression, epiphora, eye discharge, eye dryness, eye irritation, eye pain, eyelid edema, eyelid erythema, eyelid pruritus, foreign body sensation, headache, hypertension, oral dryness, somnolence, superficial punctate keratitis, and visual disturbance.

Other adverse reactions that have been reported with the individual components are listed below.

Brimonidine Tartrate (0.1%-0.2%)

Abnormal taste, allergic reaction, blepharoconjunctivitis, blurred vision, bronchitis, cataract, conjunctival blanching, conjunctival edema, conjunctival hemorrhage, conjunctivitis, cough, dizziness, dyspepsia, dyspnea, fatigue, flu syndrome, follicular conjunctivitis, gastrointestinal disorder, hypercholesterolemia, hypotension, infection (primarily colds and respiratory infections), hordeolum, insomnia, keratitis, lid crusting, lid disorder, muscular pain, nasal dryness, ocular allergic reaction, pharyngitis, photophobia, rash, rhinitis, sinus infection, sinusitis, superficial punctate keratopathy, tearing, upper respiratory symptoms, visual field defect, vitreous detachment, vitreous disorder, vitreous floaters, and worsened visual acuity.

Timolol (Ocular Administration)

Body as a whole: chest pain; Cardiovascular: Arrhythmia, bradycardia, cardiac arrest, cardiac failure, cerebral ischemia, cerebral vascular accident, claudication, cold hands and feet, edema, heart block, palpitation, pulmonary edema, Raynaud’s phenomenon, syncope, and worsening of angina pectoris; Digestive: anorexia, diarrhea, nausea; Immunologic: Systemic lupus erythematosus; Nervous System/Psychiatric: Increase in signs and symptoms of myasthenia gravis, insomnia, nightmares, paresthesia, behavioral changes and psychic disturbances including confusion, hallucinations, anxiety, disorientation, nervousness, and memory loss; Skin: Alopecia, psoriasiform rash or exacerbation of psoriasis; Hypersensitivity: Signs and symptoms of systemic allergic reactions, including anaphylaxis, angioedema, urticaria, and generalized and localized rash; Respiratory: Bronchospasm (predominantly in patients with pre-existing bronchospastic disease) [see Contraindications (4.1)], dyspnea, nasal congestion, respiratory failure, upper respiratory infections; Endocrine: Masked symptoms of hypoglycemia in diabetes patients [see Warnings and Precautions (5.7)]; Special Senses: diplopia, choroidal detachment following filtration surgery, cystoid macular edema, decreased corneal sensitivity, pseudopemphigoid, ptosis, refractive changes, tinnitus; Urogenital: Decreased libido, impotence, Peyronie’s disease, retroperitoneal fibrosis.

6.2 Postmarketing Experience

The following reactions have been identified during post-marketing use of brimonidine tartrate ophthalmic solutions, timolol ophthalmic solutions, or both in combination, in clinical practice. Because they are reported voluntarily from a population of unknown size, estimates of frequency cannot be made. The reactions, which have been chosen for inclusion due to either their seriousness, frequency of reporting, possible causal connection to brimonidine tartrate ophthalmic solutions, timolol ophthalmic solutions, or a combination of these factors, include: eyelid erythema extending to the cheek or forehead, hypersensitivity, iritis, keratoconjunctivitis sicca, miosis, nausea, skin reactions (including erythema, rash, and vasodilation), and tachycardia. In infants, apnea, bradycardia, coma, hypothermia, hypotonia, lethargy, pallor, respiratory depression, and somnolence have been reported [see Contraindications (4.3) and Use in Specific Populations (8.4)].

Oral Timolol/Oral Beta-blockers

The following additional adverse reactions have been reported in clinical experience with ORAL timolol maleate or other ORAL beta-blocking agents and may be considered potential effects of ophthalmic timolol maleate: Allergic: Erythematous rash, fever combined with aching and sore throat, laryngospasm with respiratory distress; Body as a whole: Decreased exercise tolerance, extremity pain, weight loss; Cardiovascular: Vasodilatation, worsening of arterial insufficiency; Digestive: Gastrointestinal pain, hepatomegaly, ischemic colitis, mesenteric arterial thrombosis, vomiting; Hematologic: Agranulocytosis, nonthrombocytopenic purpura, thrombocytopenic purpura; Endocrine: Hyperglycemia, hypoglycemia; Skin: Increased pigmentation, pruritus, skin irritation, sweating; Musculoskeletal: Arthralgia; Nervous System/Psychiatric: An acute reversible syndrome characterized by disorientation for time and place, decreased performance on neuropsychometrics, diminished concentration, emotional lability, local weakness, reversible mental depression progressing to catatonia, slightly clouded sensorium, vertigo; Respiratory: Bronchial obstruction, rales; Urogenital: Urination difficulties.

7 DRUG INTERACTIONS

7.1 Antihypertensives/Cardiac Glycosides

Because COMBIGAN® may reduce blood pressure, caution in using drugs such as antihypertensives and/or cardiac glycosides with COMBIGAN® is advised.

7.2 Beta-adrenergic Blocking Agents

Patients who are receiving a beta-adrenergic blocking agent either orally or intravenously and COMBIGAN® should be observed for potential additive effects of beta-blockade, both systemic and on intraocular pressure. The concomitant use of two topical beta-adrenergic blocking agents is not recommended.

7.3 Calcium Antagonists

Caution should be used in the co-administration of beta-adrenergic blocking agents, such as COMBIGAN®, and oral or intravenous calcium antagonists because of possible atrioventricular conduction disturbances, left ventricular failure, and hypotension. In patients with impaired cardiac function, co-administration should be avoided.

7.4 Catecholamine-depleting Drugs

Close observation of the patient is recommended when a beta blocker is administered to patients receiving catecholamine-depleting drugs such as reserpine, because of possible additive effects and the production of hypotension and/or marked bradycardia, which may result in vertigo, syncope, or postural hypotension.

7.5 CNS Depressants

Although specific drug interaction studies have not been conducted with COMBIGAN®, the possibility of an additive or potentiating effect with CNS depressants (alcohol, barbiturates, opiates, sedatives, or anesthetics) should be considered.

7.6 Digitalis and Calcium Antagonists

The concomitant use of beta-adrenergic blocking agents with digitalis and calcium antagonists may have additive effects in prolonging atrioventricular conduction time.

7.7 CYP2D6 Inhibitors

Potentiated systemic beta-blockade (e.g., decreased heart rate, depression) has been reported during combined treatment with CYP2D6 inhibitors (e.g., quinidine, SSRIs) and timolol.

7.8 Tricyclic Antidepressants

Tricyclic antidepressants have been reported to blunt the hypotensive effect of systemic clonidine. It is not known whether the concurrent use of these agents with COMBIGAN® in humans can lead to resulting interference with the IOP-lowering effect. Caution, however, is advised in patients taking tricyclic antidepressants which can affect the metabolism and uptake of circulating amines.

7.9 Monoamine Oxidase Inhibitors

Monoamine oxidase (MAO) inhibitors may theoretically interfere with the metabolism of brimonidine and potentially result in an increased systemic side effect such as hypotension. Caution, however, is advised in patients taking MAO inhibitors which can affect the metabolism and uptake of circulating amines.

8 USE IN SPECIFIC POPULATIONS

8.1 Pregnancy

Teratogenicity studies have been performed in animals. Brimonidine tartrate was not teratogenic when given orally during gestation days 6 through 15 in rats and days 6 through 18 in rabbits. The highest doses of brimonidine tartrate in rats (2.5 mg/kg/day) and rabbits (5 mg/kg/day) achieved AUC exposure values 580 and 37-fold higher, respectively, than similar values estimated in humans treated with COMBIGAN®, 1 drop in both eyes twice daily.

Teratogenicity studies with timolol in mice, rats, and rabbits at oral doses up to 50 mg/kg/day [4,200 times the maximum recommended human ocular dose of 0.012 mg/kg/day on a mg/kg basis (MRHOD)] demonstrated no evidence of fetal malformations. Although delayed fetal ossification was observed at this dose in rats, there were no adverse effects on postnatal development of offspring. Doses of 1,000 mg/kg/day (83,000 times the MRHOD) were maternotoxic in mice and resulted in an increased number of fetal resorptions. Increased fetal resorptions were also seen in rabbits at doses 8,300 times the MRHOD without apparent maternotoxicity.

There are no adequate and well-controlled studies in pregnant women; however, in animal studies, brimonidine crossed the placenta and entered into the fetal circulation to a limited extent. Because animal reproduction studies are not always predictive of human response, COMBIGAN® should be used during pregnancy only if the potential benefit to the mother justifies the potential risk to the fetus.

8.3 Nursing Mothers

Timolol has been detected in human milk following oral and ophthalmic drug administration. It is not known whether brimonidine tartrate is excreted in human milk, although in animal studies, brimonidine tartrate has been shown to be excreted in breast milk. Because of the potential for serious adverse reactions from COMBIGAN® in nursing infants, a decision should be made whether to discontinue nursing or to discontinue the drug, taking into account the importance of the drug to the mother.

8.4 Pediatric Use

COMBIGAN® is contraindicated in children under the age of 2 years [see Contraindications (4.3)]. During post-marketing surveillance, apnea, bradycardia, coma, hypotension, hypothermia, hypotonia, lethargy, pallor, respiratory depression, and somnolence have been reported in infants receiving brimonidine. The safety and effectiveness of brimonidine tartrate and timolol maleate have not been studied in children below the age of 2 years.

The safety and effectiveness of COMBIGAN® have been established in the age groups 2 – 16 years of age. Use of COMBIGAN® in these age groups is supported by evidence from adequate and well-controlled studies of COMBIGAN® in adults with additional data from a study of the concomitant use of brimonidine tartrate ophthalmic solution 0.2% and timolol maleate ophthalmic solution in pediatric glaucoma patients (ages 2 to 7 years). In this study, brimonidine tartrate ophthalmic solution 0.2% was dosed three times a day as adjunctive therapy to beta-blockers. The most commonly observed adverse reactions were somnolence (50%-83% in patients 2 to 6 years) and decreased alertness. In pediatric patients 7 years of age or older (>20 kg), somnolence appears to occur less frequently (25%). Approximately 16% of patients on brimonidine tartrate ophthalmic solution discontinued from the study due to somnolence.

8.5 Geriatric Use

No overall differences in safety or effectiveness have been observed between elderly and other adult patients.

10 OVERDOSAGE

There have been reports of inadvertent overdosage with timolol ophthalmic solution resulting in systemic effects similar to those seen with systemic beta-adrenergic blocking agents such as dizziness, headache, shortness of breath, bradycardia, bronchospasm, and cardiac arrest. With the exception of hypotension, very limited information exists on accidental ingestion of brimonidine in adults. Symptoms of brimonidine overdose have been reported in neonates, infants, and children receiving brimonidine ophthalmic solutions as part of medical treatment of congenital glaucoma or by accidental oral ingestion [see Use in Specific Populations (8.4)]. Treatment of an oral overdose includes supportive and symptomatic therapy; a patent airway should be maintained.

11 DESCRIPTION

COMBIGAN® (brimonidine tartrate/timolol maleate ophthalmic solution) 0.2%/0.5%, sterile, is a relatively selective alpha-2 adrenergic receptor agonist with a non-selective beta-adrenergic receptor inhibitor (topical intraocular pressure lowering agent).

The structural formulae are:

Brimonidine tartrate:

5-bromo-6-(2-imidazolidinylideneamino) quinoxaline L-tartrate; MW= 442.24

Timolol maleate:

(-)-1-(tert-butylamino)-3-[(4-morpholino-1,2,5-thiadiazol-3-yl)-oxy]-2-propanol maleate (1:1) (salt); MW= 432.50 as the maleate salt

In solution, COMBIGAN® (brimonidine tartrate/timolol maleate ophthalmic solution) 0.2%/0.5% has a clear, greenish-yellow color. It has an osmolality of 260-330 mOsmol/kg and a pH during its shelf life of 6.5-7.3.

Brimonidine tartrate appears as an off-white, or white to pale-yellow powder and is soluble in both water (1.5 mg/mL) and in the product vehicle (3 mg/mL) at pH 7.2. Timolol maleate appears as a white, odorless, crystalline powder and is soluble in water, methanol, and alcohol.

Each mL of COMBIGAN® contains the active ingredients brimonidine tartrate 0.2% and timolol 0.5% with the inactive ingredients benzalkonium chloride 0.005%; sodium phosphate, monobasic; sodium phosphate, dibasic; purified water; and hydrochloric acid and/or sodium hydroxide to adjust pH.

12 CLINICAL PHARMACOLOGY

12.1 Mechanism of Action

COMBIGAN® is comprised of two components: brimonidine tartrate and timolol. Each of these two components decreases elevated intraocular pressure, whether or not associated with glaucoma. Elevated intraocular pressure is a major risk factor in the pathogenesis of optic nerve damage and glaucomatous visual field loss. The higher the level of intraocular pressure, the greater the likelihood of glaucomatous field loss and optic nerve damage.

COMBIGAN® is a relatively selective alpha-2 adrenergic receptor agonist with a non-selective beta-adrenergic receptor inhibitor. Both brimonidine and timolol have a rapid onset of action, with peak ocular hypotensive effect seen at two hours post-dosing for brimonidine and one to two hours for timolol.

Fluorophotometric studies in animals and humans suggest that brimonidine tartrate has a dual mechanism of action by reducing aqueous humor production and increasing uveoscleral outflow.

Timolol maleate is a beta1 and beta2 adrenergic receptor inhibitor that does not have significant intrinsic sympathomimetic, direct myocardial depressant, or local anesthetic (membrane-stabilizing) activity.

12.3 Pharmacokinetics

Absorption

Systemic absorption of brimonidine and timolol was assessed in healthy volunteers and patients following topical dosing with COMBIGAN®. Normal volunteers dosed with one drop of COMBIGAN® twice daily in both eyes for seven days showed peak plasma brimonidine and timolol concentrations of 30 pg/mL and 400 pg/mL, respectively. Plasma concentrations of brimonidine peaked at 1 to 4 hours after ocular dosing. Peak plasma concentrations of timolol occurred approximately 1 to 3 hours post-dose.

In a crossover study of COMBIGAN®, brimonidine tartrate 0.2%, and timolol 0.5% administered twice daily for 7 days in healthy volunteers, the mean brimonidine area-under-the-plasma-concentration-time curve (AUC) for COMBIGAN® was 128 ± 61 pg•hr/mL versus 141 ± 106 pg•hr/mL for the respective monotherapy treatments; mean Cmax values of brimonidine were comparable following COMBIGAN® treatment versus monotherapy (32.7 ± 15 pg/mL versus 34.7 ± 22.6 pg/mL, respectively). Mean timolol AUC for COMBIGAN® was similar to that of the respective monotherapy treatment (2919 ± 1679 pg•hr/mL versus 2909 ± 1231 pg•hr/mL, respectively); mean Cmax of timolol was approximately 20% lower following COMBIGAN® treatment versus monotherapy.

In a parallel study in patients dosed twice daily with COMBIGAN®, twice daily with timolol 0.5%, or three times daily with brimonidine tartrate 0.2%, one-hour post dose plasma concentrations of timolol and brimonidine were approximately 30-40% lower with COMBIGAN® than their respective monotherapy values. The lower plasma brimonidine concentrations with COMBIGAN® appears to be due to twice-daily dosing for COMBIGAN® versus three-times dosing with brimonidine tartrate 0.2%.

Distribution

The protein binding of timolol is approximately 60%. The protein binding of brimonidine has not been studied.

Metabolism

In humans, brimonidine is extensively metabolized by the liver. Timolol is partially metabolized by the liver.

Excretion

In the crossover study in healthy volunteers, the plasma concentration of brimonidine declined with a systemic half-life of approximately 3 hours. The apparent systemic half-life of timolol was about 7 hours after ocular administration.

Urinary excretion is the major route of elimination of brimonidine and its metabolites. Approximately 87% of an orally-administered radioactive dose of brimonidine was eliminated within 120 hours, with 74% found in the urine. Unchanged timolol and its metabolites are excreted by the kidney.

Special Populations

COMBIGAN® has not been studied in patients with hepatic impairment.

COMBIGAN® has not been studied in patients with renal impairment.

A study of patients with renal failure showed that timolol was not readily removed by dialysis. The effect of dialysis on brimonidine pharmacokinetics in patients with renal failure is not known.

Following oral administration of timolol maleate, the plasma half-life of timolol is essentially unchanged in patients with moderate renal insufficiency.

13 NONCLINICAL TOXICOLOGY

13.1 Carcinogenesis, Mutagenesis, Impairment of Fertility

With brimonidine tartrate, no compound-related carcinogenic effects were observed in either mice or rats following a 21-month and 24-month study, respectively. In these studies, dietary administration of brimonidine tartrate at doses up to 2.5 mg/kg/day in mice and 1 mg/kg/day in rats achieved 150 and 210 times, respectively, the plasma Cmax drug concentration in humans treated with one drop of COMBIGAN® into both eyes twice daily, the recommended daily human dose.

In a two-year study of timolol maleate administered orally to rats, there was a statistically significant increase in the incidence of adrenal pheochromocytomas in male rats administered 300 mg/kg/day [approximately 25,000 times the maximum recommended human ocular dose of 0.012 mg/kg/day on a mg/kg basis (MRHOD)]. Similar differences were not observed in rats administered oral doses equivalent to approximately 8,300 times the daily dose of COMBIGAN® in humans.

In a lifetime oral study of timolol maleate in mice, there were statistically significant increases in the incidence of benign and malignant pulmonary tumors, benign uterine polyps and mammary adenocarcinomas in female mice at 500 mg/kg/day, (approximately 42,000 times the MRHOD), but not at 5 or 50 mg/kg/day (approximately 420 to 4,200 times higher, respectively, than the MRHOD). In a subsequent study in female mice, in which post-mortem examinations were limited to the uterus and the lungs, a statistically significant increase in the incidence of pulmonary tumors was again observed at 500 mg/kg/day.

The increased occurrence of mammary adenocarcinomas was associated with elevations in serum prolactin which occurred in female mice administered oral timolol at 500 mg/kg/day, but not at doses of 5 or 50 mg/kg/day. An increased incidence of mammary adenocarcinomas in rodents has been associated with administration of several other therapeutic agents that elevate serum prolactin, but no correlation between serum prolactin levels and mammary tumors has been established in humans. Furthermore, in adult human female subjects who received oral dosages of up to 60 mg of timolol maleate (the maximum recommended human oral dosage), there were no clinically meaningful changes in serum prolactin.

Brimonidine tartrate was not mutagenic or clastogenic in a series of in vitro and in vivo studies including the Ames bacterial reversion test, chromosomal aberration assay in Chinese Hamster Ovary (CHO) cells, and three in vivo studies in CD-1 mice: a host-mediated assay, cytogenetic study, and dominant lethal assay.

Timolol maleate was devoid of mutagenic potential when tested in vivo (mouse) in the micronucleus test and cytogenetic assay (doses up to 800 mg/kg) and in vitro in a neoplastic cell transformation assay (up to 100 mcg/mL). In Ames tests the highest concentrations of timolol employed, 5,000 or 10,000 mcg/plate, were associated with statistically significant elevations of revertants observed with tester strain TA100 (in seven replicate assays), but not in the remaining three strains. In the assays with tester strain TA100, no consistent dose response relationship was observed, and the ratio of test to control revertants did not reach 2. A ratio of 2 is usually considered the criterion for a positive Ames test.

Reproduction and fertility studies in rats with timolol maleate and in rats with brimonidine tartrate demonstrated no adverse effect on male or female fertility at doses up to approximately 100 times the systemic exposure following the maximum recommended human ophthalmic dose of COMBIGAN®.

14 CLINICAL STUDIES

Clinical studies were conducted to compare the IOP-lowering effect over the course of the day of COMBIGAN® administered twice a day (BID) to individually-administered brimonidine tartrate ophthalmic solution, 0.2% administered three times per day (TID) and timolol maleate ophthalmic solution, 0.5% BID in patients with glaucoma or ocular hypertension. COMBIGAN® BID provided an additional 1 to 3 mm Hg decrease in IOP over brimonidine treatment TID and an additional 1 to 2 mm Hg decrease over timolol treatment BID during the first 7 hours post dosing. However, the IOP-lowering of COMBIGAN® BID was less (approximately 1-2 mm Hg) than that seen with the concomitant administration of 0.5% timolol BID and 0.2% brimonidine tartrate TID. COMBIGAN® administered BID had a favorable safety profile versus concurrently administered brimonidine TID and timolol BID in the self-reported level of severity of sleepiness for patients over age 40.

16 HOW SUPPLIED/STORAGE AND HANDLING

COMBIGAN® is supplied sterile, in white opaque plastic LDPE bottles and tips, with blue high impact polystyrene (HIPS) caps as follows:

5 mL in 10 mL bottle NDC 0023-9211-05

10 mL in 10 mL bottle NDC 0023-9211-10

15 mL in 15 mL bottle NDC 0023-9211-15

Storage: Store at 15°-25°C (59°-77°F). Protect from light.

17 PATIENT COUNSELING INFORMATION

Patients with bronchial asthma, a history of bronchial asthma, severe chronic obstructive pulmonary disease, sinus bradycardia, second or third degree atrioventricular block, or cardiac failure should be advised not to take this product [see Contraindications (4.1, 4.2)].

Patients should be instructed that ocular solutions, if handled improperly or if the tip of the dispensing container contacts the eye or surrounding structures, can become contaminated by common bacteria known to cause ocular infections. Serious damage to the eye and subsequent loss of vision may result from using contaminated solutions or by inadvertent contact with the dropper tip [see Warnings and Precautions (5.10)]. Always replace the cap after using. If solution changes color or becomes cloudy, do not use. Do not use the product after the expiration date marked on the bottle.

Patients also should be advised that if they have ocular surgery or develop an intercurrent ocular condition (e.g., trauma or infection), they should immediately seek their physician's advice concerning the continued use of the present multidose container.

If more than one topical ophthalmic drug is being used, the drugs should be administered at least five minutes apart.

Patients should be advised that COMBIGAN® contains benzalkonium chloride which may be absorbed by soft contact lenses. Contact lenses should be removed prior to administration of the solution. Lenses may be reinserted 15 minutes following administration of COMBIGAN®.

As with other similar medications, COMBIGAN® may cause fatigue and/or drowsiness in some patients. Patients who engage in hazardous activities should be cautioned of the potential for a decrease in mental alertness.

Distributed by:
AbbVie Inc.
North Chicago, IL 60064

© 2024 AbbVie. All rights reserved.
COMBIGAN and its design are trademarks of Allergan, Inc., an AbbVie company.

20087190R1

PRINCIPAL DISPLAY PANEL

NDC 0023-9211-05
Combigan®
(brimonidine tartrate/timolol maleate ophthalmic solution)
0.2%/0.5%
Rx Only
5 mL
sterile